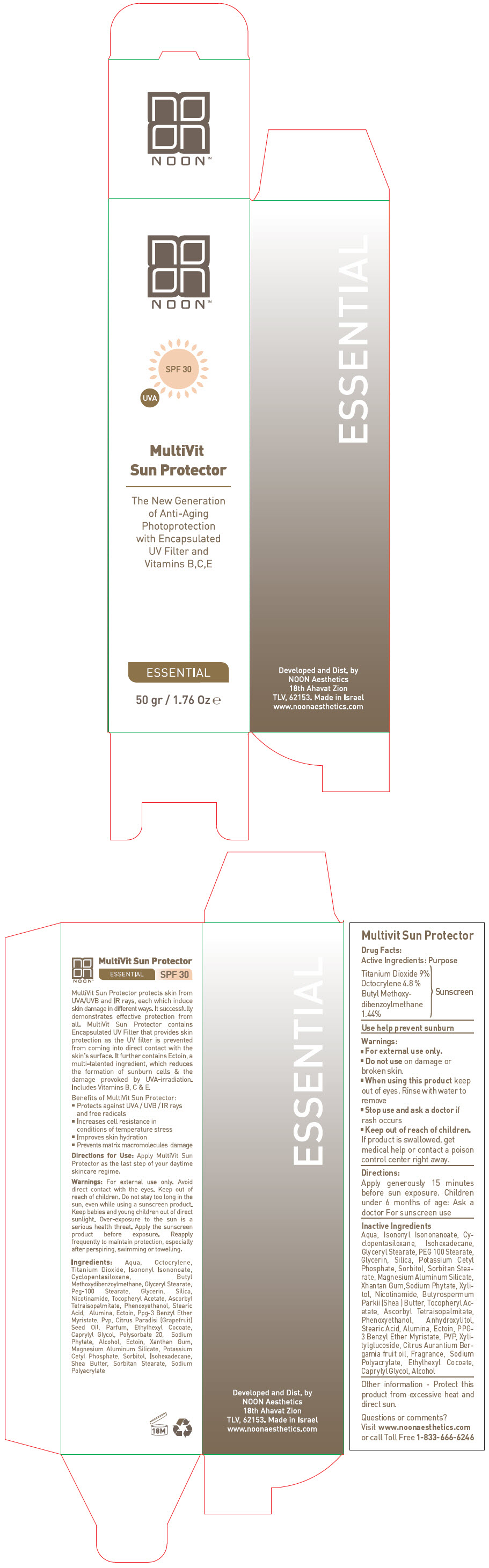 DRUG LABEL: Multivit Sun Protector
NDC: 78863-1110 | Form: CREAM
Manufacturer: Noon Aesthetics M.R. Ltd
Category: otc | Type: HUMAN OTC DRUG LABEL
Date: 20260115

ACTIVE INGREDIENTS: Titanium Dioxide 4.5 g/50 g; Octocrylene 2.4 g/50 g; AVOBENZONE 0.72 g/50 g
INACTIVE INGREDIENTS: PHYTATE SODIUM; Alcohol; Ectoine; NIACINAMIDE; GLYCERIN; XANTHAN GUM; MAGNESIUM ALUMINUM SILICATE; POTASSIUM CETYL PHOSPHATE; SORBITOL; SILICON DIOXIDE; Isohexadecane; ISONONYL ISONONANOATE; CYCLOMETHICONE 5; BERGAMOT OIL; STEARIC ACID; SHEA BUTTER; GLYCERYL MONOSTEARATE; PEG-100 MONOSTEARATE; SORBITAN MONOSTEARATE; ASCORBYL TETRAISOPALMITATE; PHENOXYETHANOL; ALUMINUM OXIDE; PPG-3 BENZYL ETHER MYRISTATE; .ALPHA.-TOCOPHEROL ACETATE; POLYSORBATE 20; POVIDONE, UNSPECIFIED; SODIUM POLYACRYLATE (2500000 MW); ETHYLHEXYL COCOATE; CAPRYLYL GLYCOL; xylitol; XYLITYLGLUCOSIDE; anhydroxylitol

Multivit Sun Protector

Drug Facts

Active Ingredients

Titanium Dioxide 9%
Octocrylene 4.8 %
Butyl Methoxydibenzoylmethane 1.44%

Purpose

Sunscreen

Use

help prevent sunburn

Warnings

- For external use only.

- Do not use on damage or broken skin.

- When using this product keep out of eyes. Rinse with water to remove

- Stop use and ask a doctor if rash occurs

- Keep out of reach of children. If product is swallowed, get medical help or contact a poison control center right away.

Directions

Apply generously 15 minutes before sun exposure. Children under 6 months of age: Ask a doctor For sunscreen use

Inactive Ingredients

Aqua, Isononyl Isononanoate, Cyclopentasiloxane, Isohexadecane, Glyceryl Stearate, PEG 100 Stearate, Glycerin, Silica, Potassium Cetyl Phosphate, Sorbitol, Sorbitan Stearate, Magnesium Aluminum Silicate, Xhantan Gum,Sodium Phytate, Xylitol, Nicotinamide, Butyrospermum Parkii (Shea) Butter, Tocopheryl Acetate, Ascorbyl Tetraisopalmitate, Phenoxyethanol, Anhydroxylitol, Stearic Acid, Alumina, Ectoin, PPG-3 Benzyl Ether Myristate, PVP, Xylitylglucoside, Citrus Aurantium Bergamia fruit oil, Fragrance, Sodium Polyacrylate, Ethylhexyl Cocoate, Caprylyl Glycol, Alcohol

Other information

Protect this product from excessive heat and direct sun.

Questions or comments?

Visit www.noonaesthetics.com or call Toll Free 1-833-666-6246

Developed and Dist. by
NOON Aesthetics
18th Ahavat Zion
TLV, 62153.

PRINCIPAL DISPLAY PANEL - 50 gr Bottle Carton

NOON™

SPF 30

UVA

MultiVit
Sun Protector

The New Generation
of Anti-Aging
Photoprotection
with Encapsulated
UV Filter and
Vitamins B,C,E

ESSENTIAL

50 gr / 1.76 Oz ℮